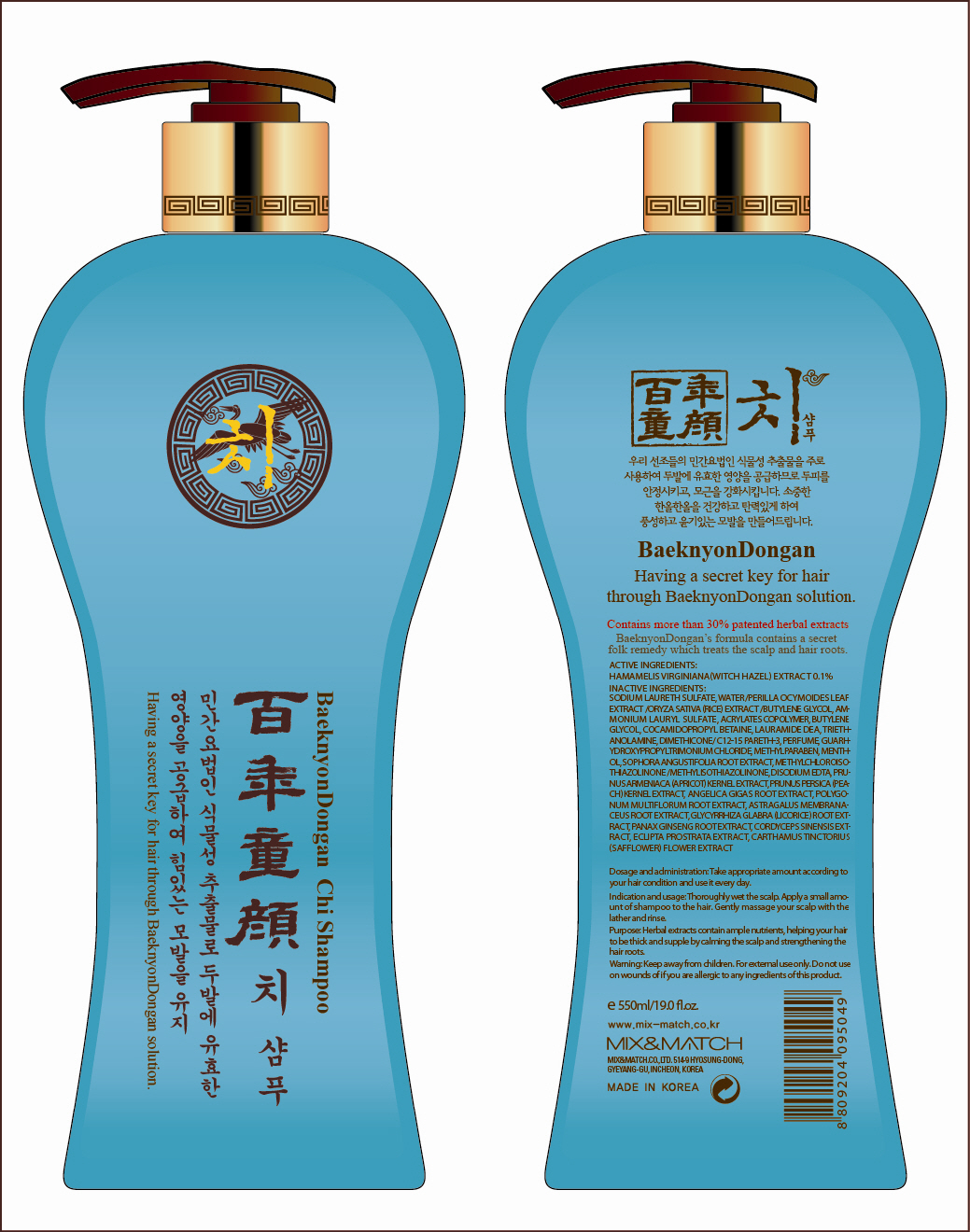 DRUG LABEL: BAEKNYONDONGAN CHI
NDC: 54948-110 | Form: SHAMPOO
Manufacturer: MIX & MATCH CO., LTD.
Category: otc | Type: HUMAN OTC DRUG LABEL
Date: 20120530

ACTIVE INGREDIENTS: WITCH HAZEL 0.55 mL/550 mL
INACTIVE INGREDIENTS: SODIUM LAURETH SULFATE; WATER; PERILLA FRUTESCENS LEAF; AMMONIUM LAURYL SULFATE; BUTYLENE GLYCOL; COCAMIDOPROPYL BETAINE; LAURIC DIETHANOLAMIDE; TROLAMINE; DIMETHICONE; METHYLPARABEN; MENTHOL; SOPHORA FLAVESCENS ROOT; METHYLCHLOROISOTHIAZOLINONE; METHYLISOTHIAZOLINONE; EDETATE DISODIUM; PRUNUS ARMENIACA SEED; PRUNUS PERSICA SEED; ANGELICA GIGAS ROOT; FALLOPIA MULTIFLORA ROOT; ASTRAGALUS PROPINQUUS ROOT; GLYCYRRHIZA GLABRA; OPHIOCORDYCEPS SINENSIS

Drug Facts

Active ingredient: WITCH HAZEL 0.1%

Inactive ingredients:
Sodium Laureth sulfate, Water, Perilla Ocymoides Leaf Extract, Oryza Sativa (Rice) Extract, Butylene Glycol, Ammonium Lauryl Sulfate, Acrylates Copolymer, Cocamidopropyl Betaine, Lauramide DEA, Triethanolamine, Dimethicone, C12-15 Pareth-3, Perfume, Guar Hydroxypropyltrimonium Chloride, Methylparaben, Menthol, Sophora Angustifolia Root Extract, Methylchloroisothiazolinone, Methylisothiazolinone, Disodium EDTA, Prunus Armeniaca (Apricot) Kernel Extract, Prunus Persica (Peach) Kernel Extract, Angelica Gigas Root Extract, Polygonum Multiflorum Root Extract, Astragalus Membranaceus Root Extract, Glycyrrhiza Glabra (Licorice) Root Extract, Panax Ginseng Root Extract, Cordyceps Sinensis Extract, Eclipta Prostrata Extract, Carthamus Tinctorius (Safflower) Flower Extract

Purpose: Skin Protectant

Warnings:
For external use only.
Do not use on wounds of if you are allergic to any ingredients of this product.

Keep out of reach of children:
Keep away from children.

Indication and usage:
Thoroughly wet the scalp.
Apply a small amount of shampoo to the hair.
Gently massage your scalp with lather and rinse.

Dosage and administration:
Take appropriate amount according to your hair condition and use it every day.